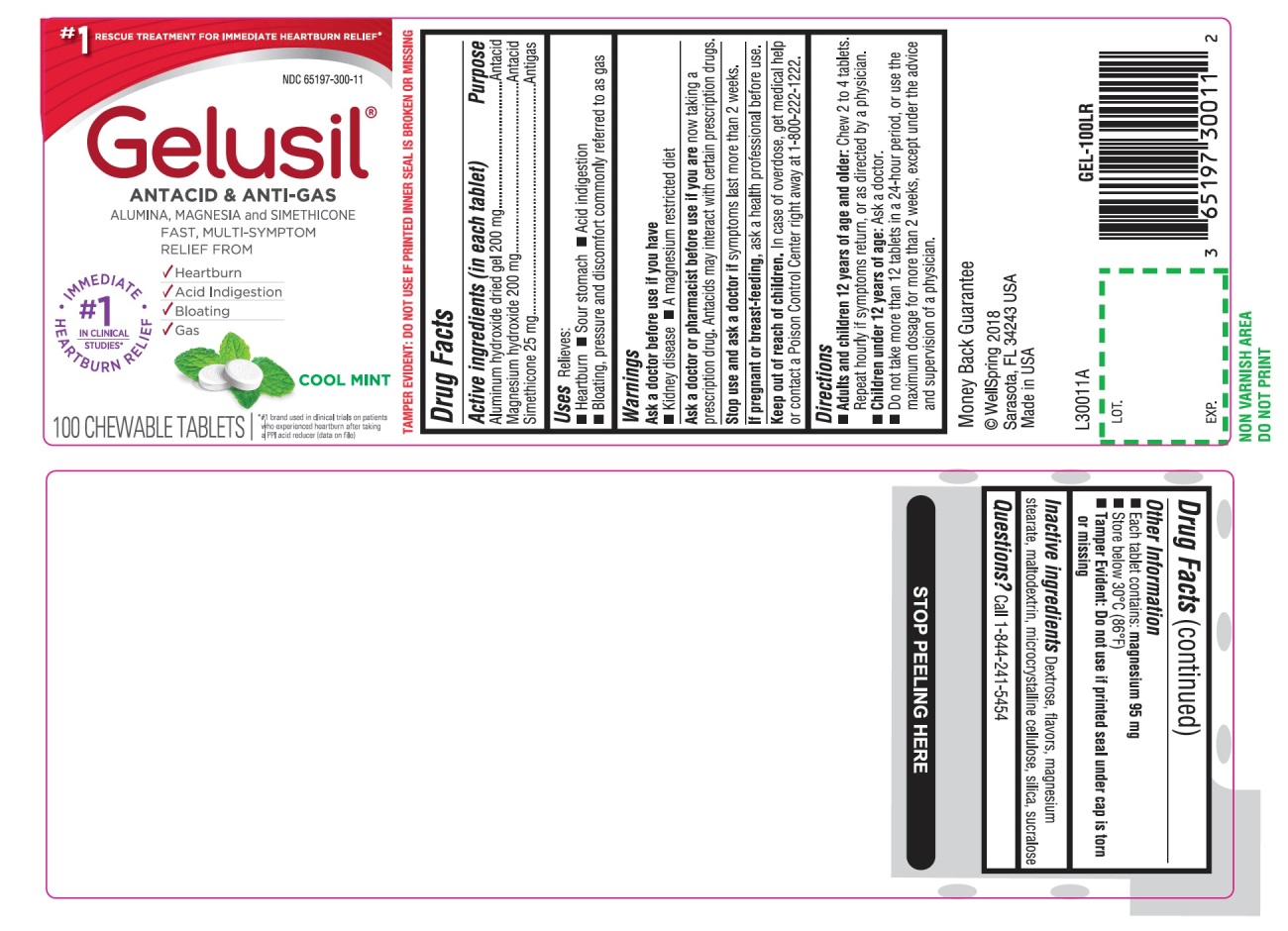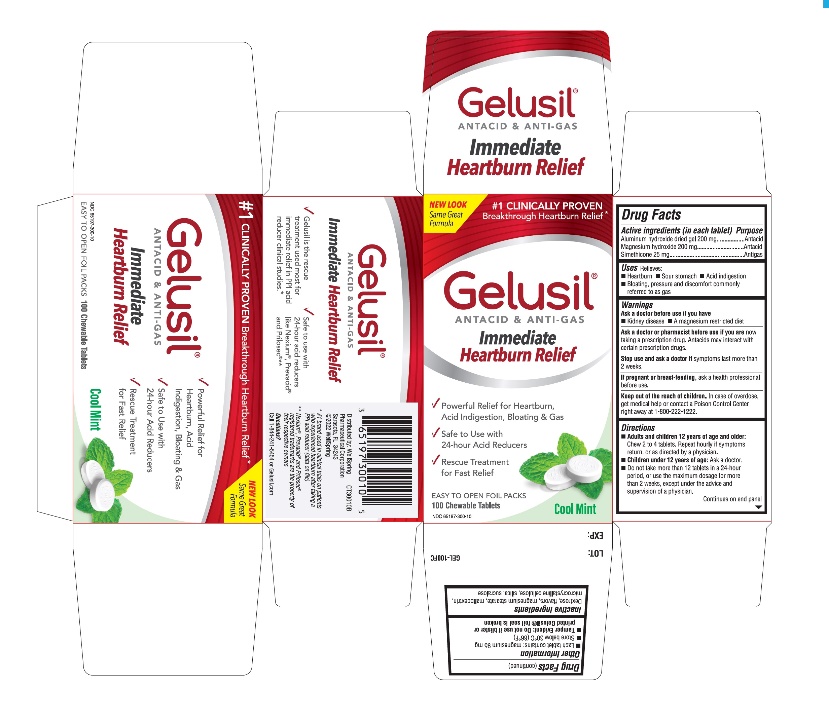 DRUG LABEL: Gelusil
NDC: 65197-300 | Form: TABLET, CHEWABLE
Manufacturer: WellSpring Pharmaceutical Corporation
Category: otc | Type: HUMAN OTC DRUG LABEL
Date: 20251120

ACTIVE INGREDIENTS: ALUMINUM HYDROXIDE 200 mg/1 1; MAGNESIUM HYDROXIDE 200 mg/1 1; DIMETHICONE, UNSPECIFIED 24 mg/1 1; SILICON DIOXIDE 1 mg/1 1
INACTIVE INGREDIENTS: DEXTROSE, UNSPECIFIED FORM; MAGNESIUM STEARATE; MALTODEXTRIN; SUCRALOSE; SILICON; MICROCRYSTALLINE CELLULOSE

Gelusil Tablets

Active Ingredients (in each tablet)

Aluminum hydroxide dried gel 200 mg
Magnesium hydroxide 200 mg
Simethicone 25 mg

Purpose

Active ingredients (in each tablet) Purpose
Aluminum hydroxide dried gel 200 mg........................Antacid
Magnesium hydroxide 200 mg....................................Antacid
Simethicone 25 mg......................................................Antigas

Uses

Relieves:

- Heartburn
- Sour stomach
- Acid indigestion
- Bloating, pressure and discomfort commonly referred to as gas

Warnings

Ask a doctor before use if you have

- Kidney disease
- A magnesium restricted diet

Ask a doctor or pharmacist before use if you are

now taking a prescription drug. Antacids may interact with certain prescription drugs.

Stop use and ask a doctor if

symptoms last more than 2 weeks

Keep out of reach of children.

In case of overdose, get medical help or contact a Poison Control Center right away 1.800.222.1222

If pregnant or breastfeeding

ask a health professional before use.

Directions

- Adults and children 12 years of age and older:Chew 2 to 4 tablets. Repeat hourly if symptoms return, or as directed by a physician
- Children under 12 of age:ask a doctor
- Do not take more than 12 tablets in a 24-hour period, or use the maximum dosage for more than 2 weeks, except under the advice and supervision of a physician

Other information

- Each tablet contains: magnesium 95 mg
- Store below 30°C (86°F)
- Tamper Evident. Do not use if blister or printed Gelusil foil seal is broken
- See end panel for lot number and expiration date

Inactive ingredients

Dextrose, flavors, magnesium stearate, maltodextrin, microcrystalline cellulose, silica, sucralose

Questions?

Call 1-844-241-5454

© WellSpring 2018

Sarasota, FL 34243 USA

Made in USA